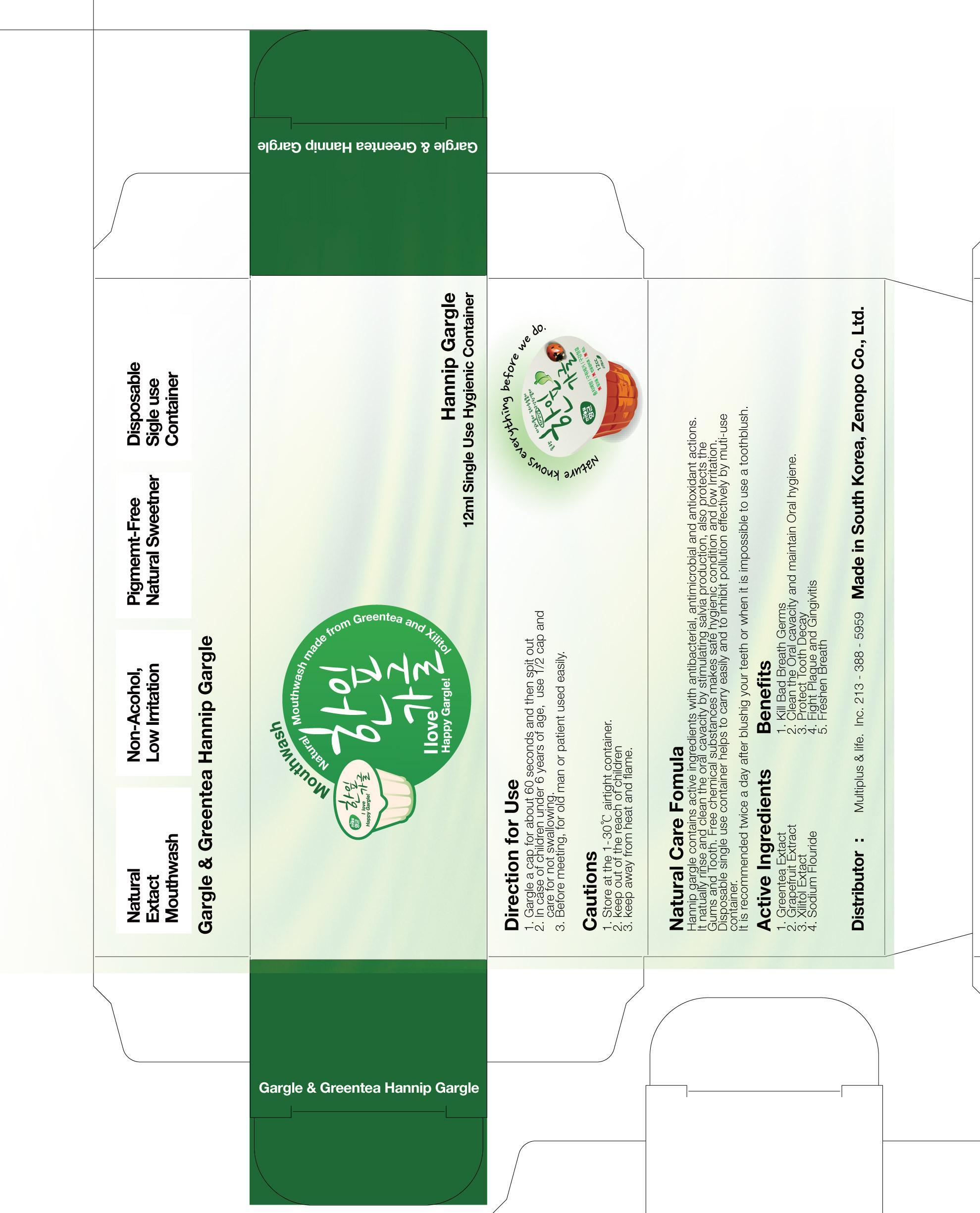 DRUG LABEL: Hanip Gargle pine fragrance
NDC: 59303-2001 | Form: MOUTHWASH
Manufacturer: PISHONANC Co, Ltd
Category: otc | Type: HUMAN OTC DRUG LABEL
Date: 20130713

ACTIVE INGREDIENTS: Sodium Fluoride 20 mg/100000 mL
INACTIVE INGREDIENTS: GREEN TEA LEAF; XYLITOL; GRAPEFRUIT; APPLE; PEPPERMINT; SODIUM BENZOATE

Drug Facts

ACTIVE INGREDIENT

sodium fluoride

INACTIVE INGREDIENT

green tea extract, xylitol, grape fruit extract, apple fragrance, peppermint fragrance, sodium beozoate

PURPOSE

dental care

keep out of reach of the children

INDICATIONS AND USAGE

- gargle a cap for about 60 seconds and then spit out
- in case of children under 6 years of age, use 1/2 cap and care for not swallowing
- before meeting, for old man or patient used easily

WARNINGS

keep away from heat and flame

DOSAGE AND ADMINISTRATION

for dental use only